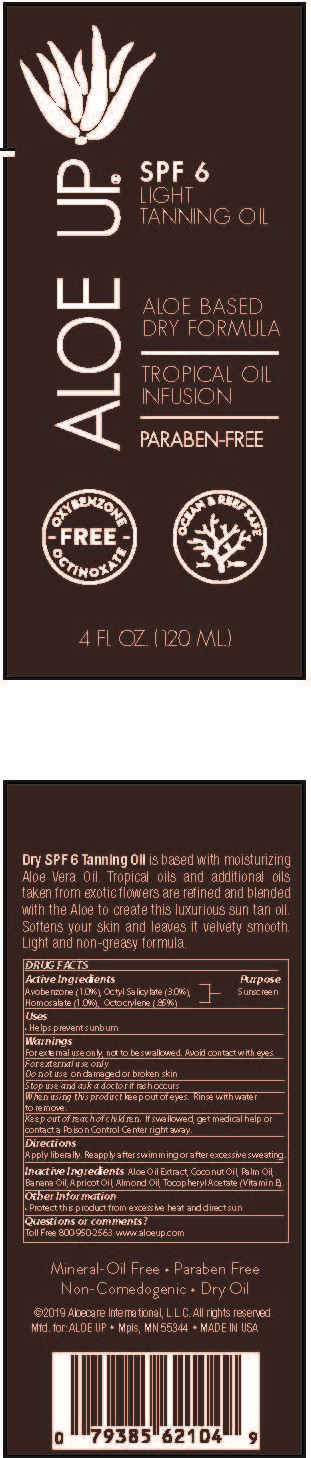 DRUG LABEL: ALOE UP LIGHT TANNING OIL
NDC: 61477-226 | Form: SPRAY
Manufacturer: Aloe Care International, LLC
Category: otc | Type: HUMAN OTC DRUG LABEL
Date: 20240213

ACTIVE INGREDIENTS: AVOBENZONE 1 g/100 mL; OCTISALATE 3 g/100 mL; HOMOSALATE 1 g/100 mL; OCTOCRYLENE 0.85 g/100 mL
INACTIVE INGREDIENTS: PALM OIL; BANANA; APRICOT KERNEL OIL; ALMOND OIL; .ALPHA.-TOCOPHEROL ACETATE; COCONUT OIL; ALOE VERA LEAF

ALOE UP - LIGHT TANNING OIL SPF-6 (61477-226)

ACTIVE INGREDIENTS:

Avobenzone (1.0%)

Octyl Salicylate (3.0%)

Homosalate (1.0%)

Octocrylene (.85%)

PURPOSE:

SUNSCREEN

USES

HELPS PREVENT SUNBURN.

DIRECTIONS:

• Apply liberally. Reapply after swimming or after excessive sweating.

Keep out of reach of children. If swallowed, get medical help or contact a Poison Control Center right away.

WARNINGS:

Skin Cancer/Skin Aging Alert: Spending time in the sun increases your risk of skin cancer and early skin aging. This product has been shown only to prevent sunburn, not skin cancer or early skin aging.
For external use only.
Do not use on damaged or broken skin.
When using this product keep out of eyes. Rinse with water to remove.
Keep away from face to avoid breathing it. Contents under pressure - do not puncture or incinerate. Do not store at temperatures above 120°F.
Stop use and ask a doctor if rash occurs
Flammable: Do not use near heat, flame or while smoking.

INACTIVE INGREDIENTS

Aloe Oil Extract, Coconut Oil, Palm Oil, Banana Oil, Apricot Oil, Almond Oil, Tocopheryl Acetate (Vitamin E).

OTHER INFORMATION

• Protect this product from excessive heat and direct sun

Questions or comments?

Toll Free 800-950-2563 www.aloeup.com